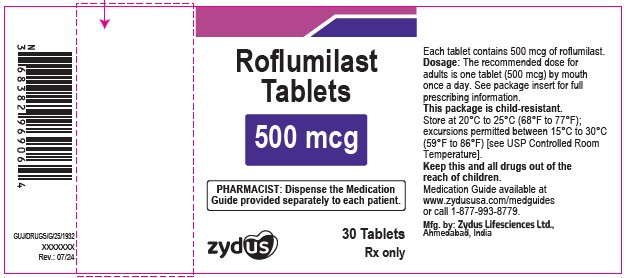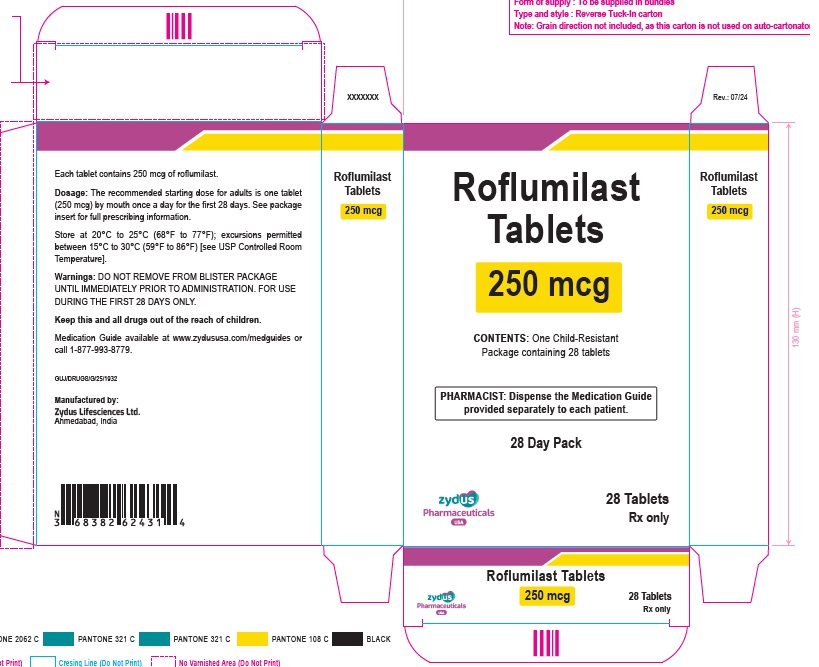 DRUG LABEL: Roflumilast
NDC: 70771-1674 | Form: TABLET
Manufacturer: Zydus Lifesciences Limited
Category: prescription | Type: HUMAN PRESCRIPTION DRUG LABEL
Date: 20240812

ACTIVE INGREDIENTS: ROFLUMILAST 500 ug/1 1
INACTIVE INGREDIENTS: CELLULOSE, MICROCRYSTALLINE; HYDROXYPROPYL CELLULOSE, LOW SUBSTITUTED; LACTOSE MONOHYDRATE; MAGNESIUM STEARATE; POLOXAMER 407; SILICON DIOXIDE; STARCH, CORN

Roflumilast Tablets, for oral use

PACKAGE LABEL.PRINCIPAL DISPLAY PANEL

NDC 70771-1674-3

Roflumilast Tablets, 500 mcg

30 tablets

Rx only

NDC 70771-1673-8

Roflumilast Tablets, 250 mcg

Blister pack of 28 tablets

Rx only